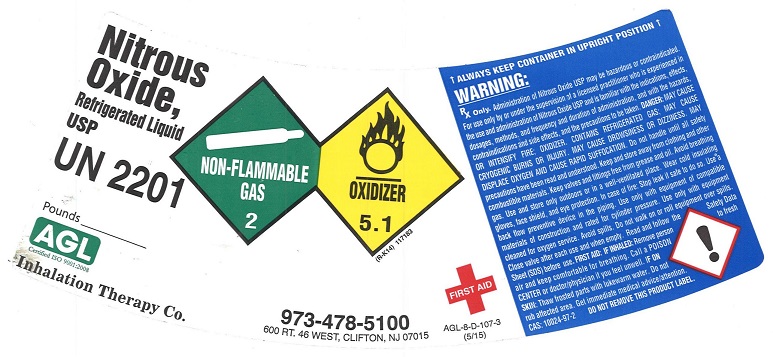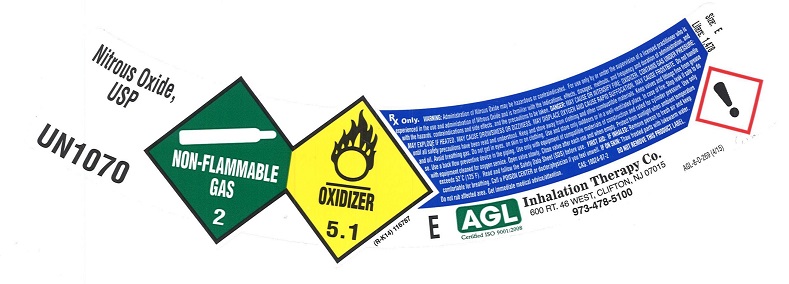 DRUG LABEL: Nitrous Oxide
NDC: 17575-011 | Form: GAS
Manufacturer: AGL Welding Supply Co., Inc.
Category: prescription | Type: HUMAN PRESCRIPTION DRUG LABEL
Date: 20260101

ACTIVE INGREDIENTS: NITROUS OXIDE 990 mL/1 L

nitrous oxide

PACKAGE LABEL

Nitrous Oxide, Refrigerated Liquid USP UN2201 NON-FLAMMABLE GAS 2 OXIDIZER 5.1
AGL Certified ISO 9001:2008 Inhalation Therapy Co. 973-478-5100 600 RT. 46 WEST, CLIFTON, NJ 07015
ALWAYS KEEP CONAINER IN UPRIGHT POSITION
WARNING: Rx only. Administration of Nitrous Oxide may be hazardous or contraindicated. For use only by or under the supervision of a licensed practitioner who is experienced in the use and administration of Nitrous Oxide and is familiar with the indications, effects, dosages, methods, and frequency and duration of administration, and with the hazards, contraindications and side effects, and the precautions to be taken. DANGER: MAY CAUSE OR INTENSIFY FIRE; OXIDIZER CONTAINS REFRIGERATED GAS; MAY CAUSE CRYOGENIC BURNS OR INJURY. MAY CAUSE DROWSINESS OR DIZZINESS. MAY DISPLACE OXYGEN AND CAUSE RAPID SUFFOCATION. Do not handle until all safety precautions have been read and understood. Keep and store away from clothing and other combustible materials. Keep valves and fittings free from grease and oil. Avoid breathing gas. Use and store only outdoors or in a well-ventilated place. Wear cold insulating gloves, face shield, and eye protection. In case of fire: stop leak if safe to do so. Use a back flow preventive device in the piping. Use only with equipment of compatible materials of construction and rated for cylinder pressure. Use only with equipment cleaned for oxygen service. Avoid spills. Do not walk on or roll equipment over spills. Close valve after each use and when empty. Read and follow the Safety Data Sheet (SDS) before use. FIRST AID FIRST AID: IF INHALED: Remove person to fresh air and keep comfortable for breathing. Call a POISON CENTER or doctor/physician if you feel unwell. IF ON SKIN: Thaw frosted parts with lukewarm water. Do not rub affected area. Get immediate medical advice/attention. CAS: 10024-97-2 DO NOT REMOVE THIS LABEL.

PACKAGE LABEL

NITROUS OXIDE, USP UN1070 NON-FLAMMABLE GAS 2 OXIDIZER 5.1
Rx only. WARNING: Administration of Nitrous Oxide may be hazardous or contraindicated. For use only by or under the supervision of a licensed practitioner who is experienced in the use and administration of Nitrous Oxide and is familiar with the indications, effects, dosages, methods, and frequency and duration of administration, and with the hazards, contraindications and side effects, and the precautions to be taken. DANGER: MAY CAUSE OR INTENSIFY FIRE; OXIDIZER CONTAINS GAS UNDER PESSURE; MAY EXPLODE IF HEATED. MAY CAUSE DROWSINESS OR DIZZINESS. MAY DISPLACE OXYGEN AND CAUSE RAPID SUFFOCATION. MAY CAUSE FROSTBITE. Do not handle until all safety precautions have been read and understood. Keep and store away from clothing and other combustible materials. Keep valves and fittings free from grease and oil. Avoid breathing gas. Do not put in eyes on skin or on clothing. Use and store only outdoors or in a well-ventilated place. In case of fire: stop leak if safe to do so. Use a back flow preventive device in the piping. Use only with equipment of compatible materials of construction and rated for cylinder pressure. Use only with equipment cleaned for oxygen service. Open valve slowly. Close valve after each use and when empty. Protect from sunlight when ambient temperature exceeds 52 degrees C (125 degrees F). Read and follow the Safety Data Sheet (SDS) before use. FIRST AID: IF INHALED: Remove person to fresh air and keep comfortable for breathing. Call a POISON CENTER or doctor/physician if you feel unwell. IF ON SKIN: Thaw frosted parts with lukewarm water. Do not rub affected area. Get immediate medical advice/attention.
CAS: 10024-97-2 DO NOT REMOVE THIS LABEL. Size: E Liters: 1,478 E
AGL Certified ISO 9001:2008 Inhalation Therapy Co. 600 RT. 46 WEST, CLIFTON, NJ 07015 973-478-5100